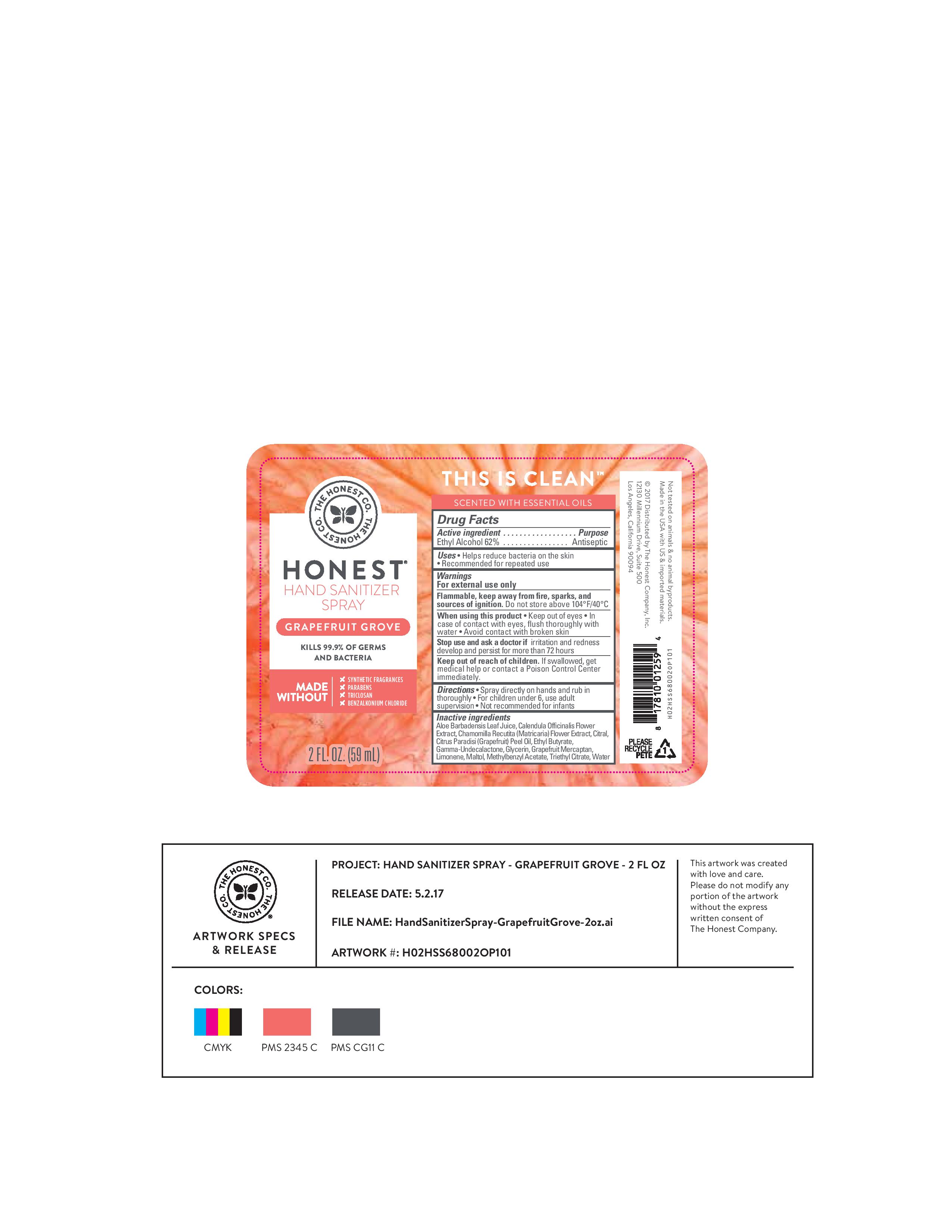 DRUG LABEL: Hand Sanitizer
NDC: 69366-312 | Form: SPRAY
Manufacturer: The Honest Company
Category: otc | Type: HUMAN OTC DRUG LABEL
Date: 20241219

ACTIVE INGREDIENTS: ALCOHOL 62 mL/100 mL
INACTIVE INGREDIENTS: ALOE VERA LEAF; CALENDULA OFFICINALIS FLOWER; ETHYL BUTYRATE; .GAMMA.-UNDECALACTONE; WATER; GLYCERIN; CHAMOMILE; CITRAL; GRAPEFRUIT OIL; 1-P-MENTHENE-8-THIOL; LIMONENE, (+)-; MALTOL; METHYLBENZYL ACETATE; TRIETHYL CITRATE

Honest Company Hand Sanitizer Spray Grapefruit Grove 2 oz

Active Ingredient

Ethyl Alcohol 62%

Purpose

Antiseptic

Uses

Helps reduce bacteria on the skin

Recommended for repeated use

Warnings

For external use only

Flammable, keep away from fire, sparks, and sources of ignition. Do not store above 104 oF/40oC

When using this product keep out of eyes. In case of contact with eyes, flush thoroughly with water. Avoid contact with broken skin

Stop use and ask a doctor if irritation and redness develop and persist for more than 72 hours

Keep out of reach of children. If swallowed, get medical help or contact a Poison Control Center immediately.

Directions

Spray directly on hands and rub in thoroughly

For children under 6, use adult supervision.

Not recommended for infants

Inactive ingredients

Aloe Barbadensis Leaf Juice, Calendula Officinalis Flower Extract, Chamomilla Recutita (Matricaria) Flower Extract, Citral, Citrus Paradisi (Grapefruit) Peel Oil, Ethyl Butyrate, Gamma-Undecalactone, Glycerin, Grapefruit Mercaptan, Limonene, Maltol, Methylbenzyl Acetate, Triethyl Citrate, Water